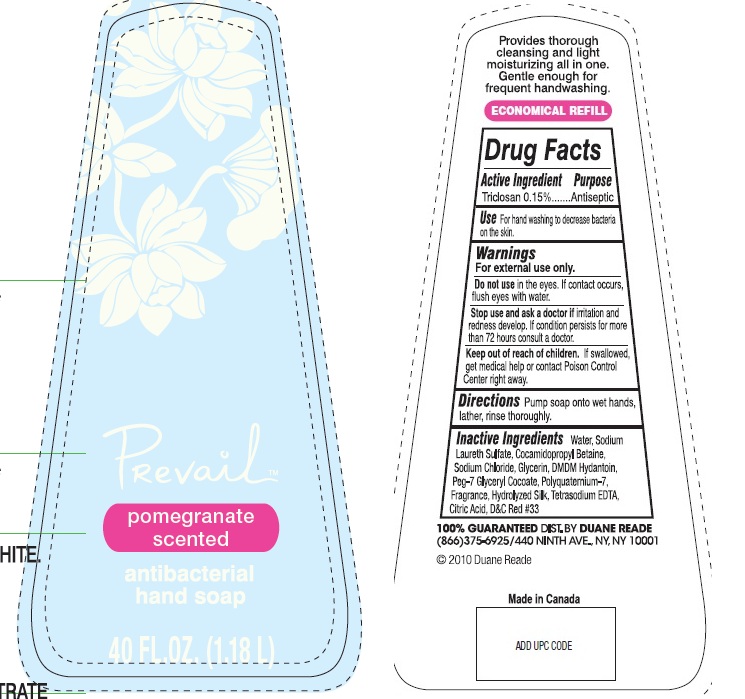 DRUG LABEL: Prevail Pomegranate Scented Antibacterial Hand
NDC: 67732-300 | Form: SOAP
Manufacturer: Duane Reade
Category: otc | Type: HUMAN OTC DRUG LABEL
Date: 20110412

ACTIVE INGREDIENTS: TRICLOSAN 0.15 L/100 L
INACTIVE INGREDIENTS: WATER; SODIUM LAURETH SULFATE; COCAMIDOPROPYL BETAINE; SODIUM CHLORIDE; GLYCERIN; DMDM HYDANTOIN; GLYCERYL COCOATE; BOMBYX MORI FIBER; EDETATE SODIUM; CITRIC ACID MONOHYDRATE; D&C RED NO. 33

Prevail Pomegranate Scented Hand Soap

Active Ingredient

Triclosan 0.15%

Purpose

Antiseptic

Use

For hand washing to decrease bacteria on the skin

Warnings

For external use only.

Do not use

in the eyes. If contact occurs, flush eyes with water

Stop use and ask a doctor

if irritation and redness develop. If condition persists for more than 72 hours consult a doctor.

Keep out of reach of children

If swallowed, get medical help or contact Poison Control Center right away

Directions

Pump soap onto wet hands, lather, rinse thoroughly

Inactive Ingredients

Water, Sodium Laureth Sulfate, Cocamidopropyl Betaine, Sodium Chloride, Glycerin, DMDM Hydantoin, Peg-7Glyceryl Cocoate, Polyquaternium-7, Fragrance, Hydrolyzed Silk, Tetrasodium EDTA, Citric Acid, FDandC yellow #5, FDandC Blue #1

DESCRIPTION

Provides thorough cleansing and light moisturizing all in one. Gentle enough for frequent handwashing.

Economical refill

100% Guaranteed Dist By Duane Reade

(866) 375-6925/440 Ninth Ave., NY, NY 10001

(c) 2010 Duane Reade

Made In Canada

PACKAGE LABEL

Prevail

pomegranate
scented

antibacterial
hand soap

40fl oz (1.18L)